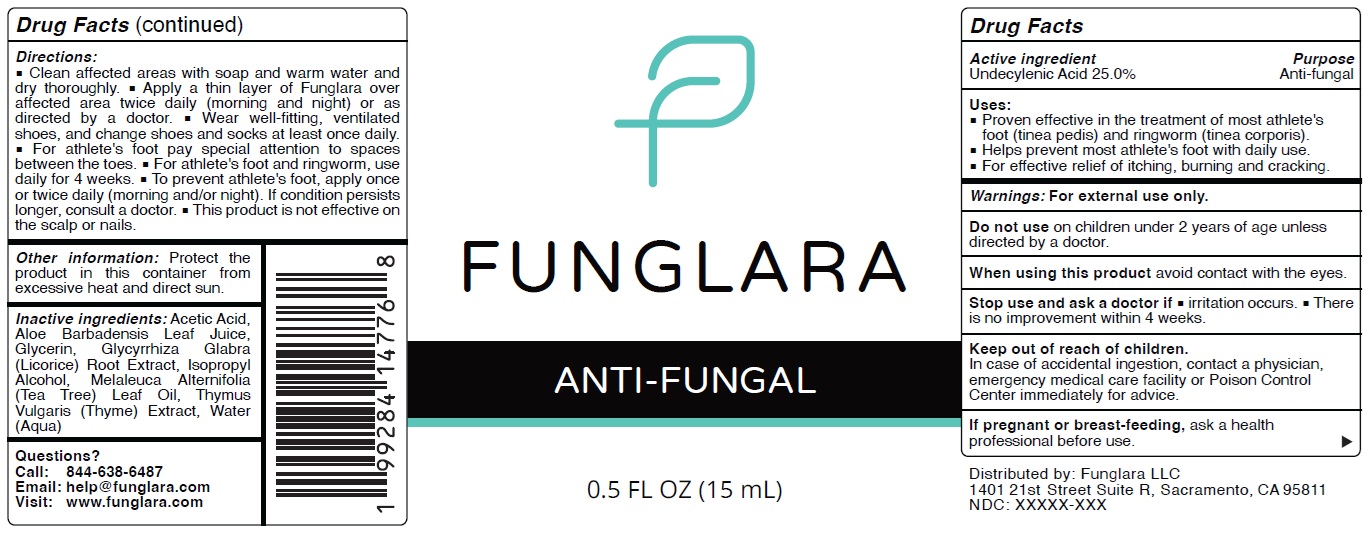 DRUG LABEL: FUNGLARA Anti Fungal
NDC: 87028-876 | Form: SOLUTION
Manufacturer: FUNGLARA LLC
Category: otc | Type: HUMAN OTC DRUG LABEL
Date: 20250820

ACTIVE INGREDIENTS: UNDECYLENIC ACID 250 mg/1 mL
INACTIVE INGREDIENTS: ACETIC ACID; ALOE VERA LEAF JUICE; GLYCERIN; GLYCYRRHIZA GLABRA (LICORICE) ROOT POWDER; ISOPROPYL ALCOHOL; TEA TREE OIL; THYME; WATER

FUNGLARA Anti Fungal

Active ingredient

Undecylenic Acid 25.0%

Purpose

Anti-fungal

Uses:

- Proven effective in the treatment of most athlete's foot (tinea pedis) and ringworm (tinea corporis).
- Helps prevent most athlete's foot with daily use.
- For effective relief of itching, burning and cracking.

Warnings:

For external use only.

Do not use

on children under 2 years of age unless directed by a doctor.

When using this product

avoid contact with the eyes.

Stop use and ask a doctor if

- irritation occurs.
- There is no improvement within 4 weeks.

Keep out of reach of children.

In case of accidental ingestion, contact a physician, emergency medical care facility or Poison Control Center immediately for advice.

If pregnant or breast-feeding,

ask a health professional before use.

Directions:

• Clean affected areas with soap and warm water and dry thoroughly. • Apply a thin layer of Funglara over affected area twice daily (morning and night) or as directed by a doctor. • Wear well-fitting, ventilated shoes, and change shoes and socks at least once daily. • For athlete's foot pay special attention to spaces between the toes. • For athlete's foot and ringworm, use daily for 4 weeks. • To prevent athlete's foot, apply once
or twice daily (morning and/or night). If condition persists longer, consult a doctor. • This product is not effective on the scalp or nails.

Other information:

Protect the product in this container from excessive heat and direct sun.

Inactive ingredients:

Acetic Acid, Aloe Barbadensis Leaf Juice, Glycerin, Glycyrrhiza Glabra (Licorice) Root Extract, Isopropyl Alcohol, Melaleuca Alternifolia (Tea Tree) Leaf Oil, Thymus Vulgaris (Thyme) Extract, Water (Aqua)

Questions?

Call: 844-638-6487
Email: help@funglara.com
Visit: www.funglara.com